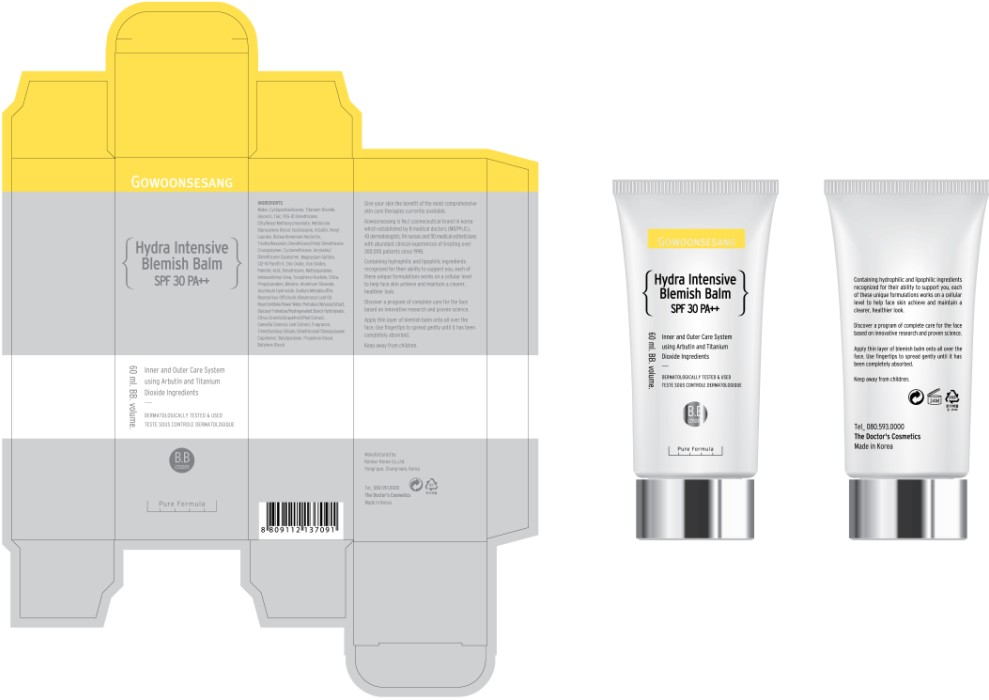 DRUG LABEL: Hydra Intensive Blemish Balm SPF30 PA
NDC: 43948-7001 | Form: CREAM
Manufacturer: The Doctor's Cosmetic Inc
Category: otc | Type: HUMAN OTC DRUG LABEL
Date: 20091001

ACTIVE INGREDIENTS: TITANIUM DIOXIDE 3 mL/60 mL; OCTINOXATE 1.8 mL/60 mL; ZINC OXIDE 0.3 mL/60 mL

ACTIVE INGREDIENTS:

Titanium Dioxide, Ethylhexyl Methoxycinnamate, Zinc Oxide, Rosmarinus Officinalis (Rosemary) Leaf Oil, Portulaca Oleracea Extract, Citrus Grandis (Grapefruit) Peel Extract, Camellia Sinensis Leaf Extract

CAUTION: Keep away from children.

WHEN USING

DIRECTION OF USE:

Apply thin layer of blemish balm onto all over the face. Use fingertips to spread gently until it has been completely absorbed.

PACKAGE LABEL

Label18c